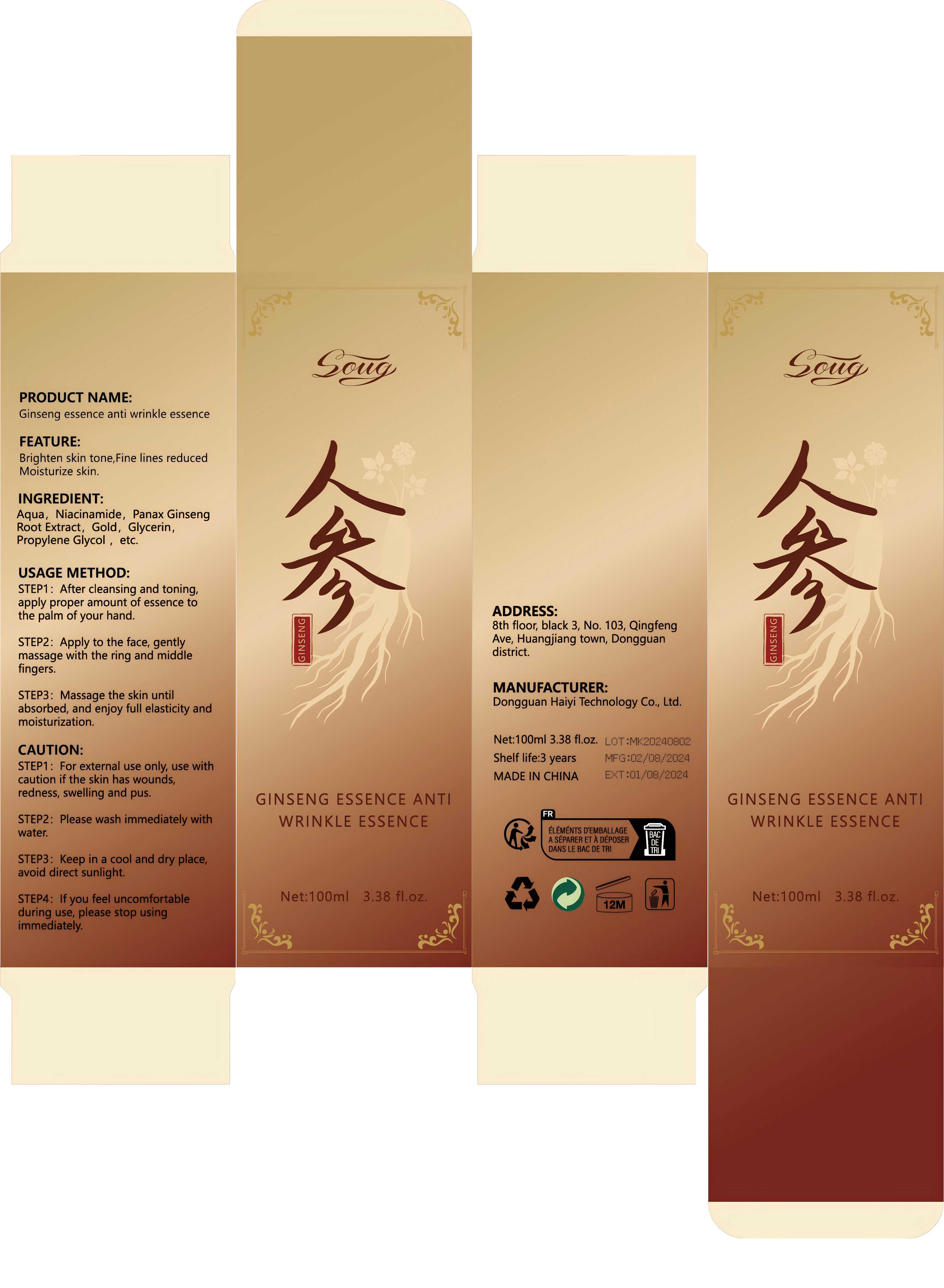 DRUG LABEL: Ginsengessence anti wrinkle essence
NDC: 84732-002 | Form: LIQUID
Manufacturer: Dongguan Haiyi Technology Co.,Ltd.
Category: otc | Type: HUMAN OTC DRUG LABEL
Date: 20240919

ACTIVE INGREDIENTS: NIACINAMIDE 2 mg/100 mL; GOLD 2 mg/100 mL; PANAX GINSENG ROOT WATER 2 mg/100 mL
INACTIVE INGREDIENTS: GLYCERIN; WATER; DIPROPYLENE GLYCOL

Active ingredient

Niacinamide

Panax Ginseng Root Extract

Gold

Inactive ingredient

Aqua

Glycerin

Propylene Glycol

Purpose section

Brighten skin tone,Fine lines reducedMoisturize skin.

WARNING

STEP1: For external use only, use withcaution if the skin has wounds,redness, swelling and pus.
STEP2: Please wash immediately withwater.
STEP3: Keep in a cool and dry place,avoid direct sunlight.
STEP4: lf you feel uncomfortableduring use, please stop usingimmediately.

stop use

if have the severe allergic reaction stop to use

not use

Pregnant women or severe skin diseases not to use

OUT OF CHILDREN

KEEP THE PRODUCT OUT OF REACH OF CHILDREN to

HOW TO USE

STEP1: After cleansing and toning,apply proper amount of essence tothe palm of your hand.
STEP2: Apply to the face, gentlymassage with the ring and middlefingers.
STEP3: Massage the skin untilabsorbed, and enjoy full elasticity andmoisturization.

Dosage

take an appropriateamount,Use 2-3 times a week